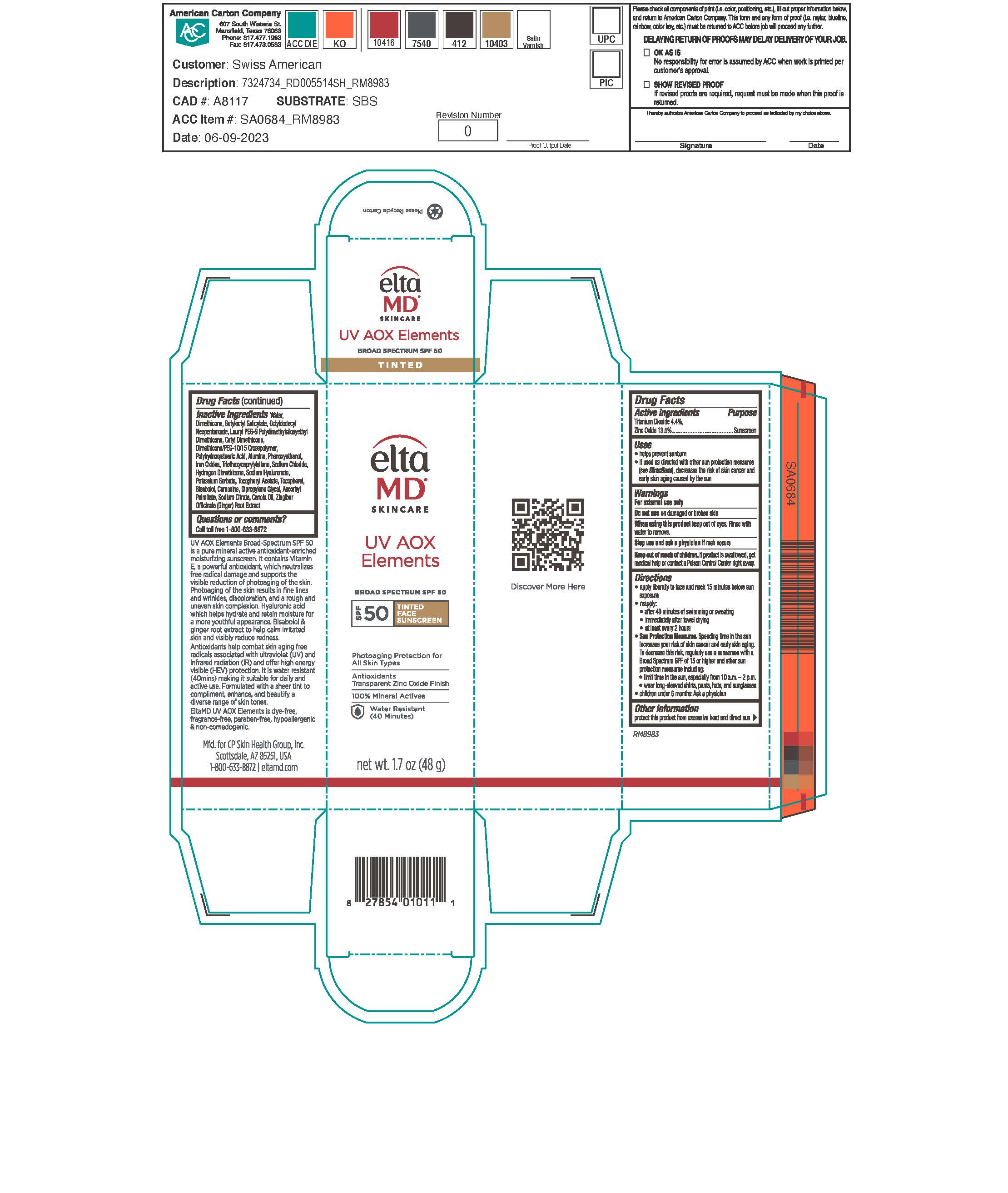 DRUG LABEL: EltaMD Skincare UV AOX Elements SPF50 Tinted
NDC: 72043-2519 | Form: LOTION
Manufacturer: CP Skin Health Group, Inc
Category: otc | Type: HUMAN OTC DRUG LABEL
Date: 20231114

ACTIVE INGREDIENTS: TITANIUM DIOXIDE 44 g/1000 g; ZINC OXIDE 135 g/1000 g
INACTIVE INGREDIENTS: WATER; DIMETHICONE; BUTYLOCTYL SALICYLATE; OCTYLDODECYL NEOPENTANOATE; LAURYL PEG-9 POLYDIMETHYLSILOXYETHYL DIMETHICONE; CETYL DIMETHICONE 25; DIMETHICONE/PEG-10/15 CROSSPOLYMER; POLYHYDROXYSTEARIC ACID (2300 MW); PHENOXYETHANOL; TRIETHOXYCAPRYLYLSILANE; SODIUM CHLORIDE; HYDROGEN DIMETHICONE (30 CST); HYALURONIC ACID; POTASSIUM SORBATE; .ALPHA.-TOCOPHEROL ACETATE; TOCOPHEROL; CARNOSINE; DIPROPYLENE GLYCOL; ASCORBYL PALMITATE; SODIUM CITRATE; CANOLA OIL; ZINGIBER OFFICINALE WHOLE; FERRIC OXIDE YELLOW; FERRIC OXIDE RED; FERROSOFERRIC OXIDE; ALUMINUM OXIDE

EltaMD Skincare UV AOX Elements SPF50 Tinted

Warnings

For external use only. Do not use on damaged or broken skin. When using this product keep out of eyes. Rinse with water to remove. Stop use and ask a physician if rash occurs. If product is swallowed get medical help or contact a Poison Control Center right away.

Uses

Helps prevent sunburn. If used as directed with other sun protection measure (See Directions), decreases the risk of skin cancer and early skin aging caused by the sun.

Purpose

Sunscreen

Active Ingredients

Titanium Dioxide 4.4%
Zinc Oxide 13.5%

Keep out of reach of children

Directions

Apply liberally 15 minutes before sun exposure. Reapply after 80 minutes of swimming or sweating, immediately after towel drying and at least every 2 hours. Sun Protection Measures: Spending time in the sun increases your risk of skin cancer and early skin aging. To decrease this risk, regularly use a sunscreen with a broad-spectrum SPF of 15 or higher and other sun protection measures including: limit time in the sun, especially from 10 am to 2 pm. Wear long-sleeve shirts, pants, hats, and sunglasses. Children under 6 months: ask a physician.

Other information:

Protect this product from excessive heat and direct sun.

QUESTIONS

call toll free 1-800-633-8872

Inactive ingredients

Water, Dimethicone, Butyloctyl Salicylate, Octyldodecyl Neopentanoate, lauryl PEG-9 polydimethylsiloxyethyl dimethicone, cetyl dimethicone, dimethicone PEG-10/15 crosspolymer,Polyhydroxystearic Acid, alumina, phenoxyethanol, iron oxides, Triethoxycaprylylsilane, sodium chloride, hydrogen dimethicone, sodium hyaluronate, potassium sorbate, Tocopheryl Acetate, tocopherol, bisabolol, carnosine, dipropylene glycol, ascorbyl palmitate, soidum citrate, canola oil, zingiber officinale (giner) root extract